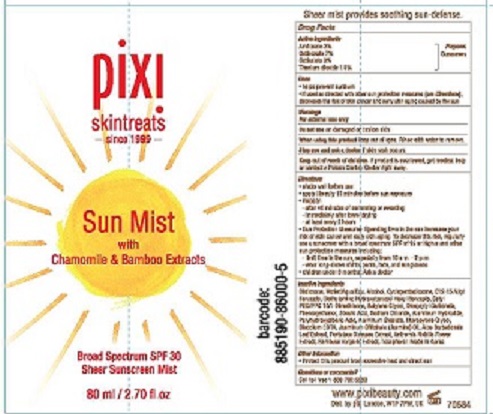 DRUG LABEL: PIXI SUN MIST SPF 30
NDC: 70686-101 | Form: SPRAY
Manufacturer: PIXI, INC
Category: otc | Type: HUMAN OTC DRUG LABEL
Date: 20181108

ACTIVE INGREDIENTS: AMILOXATE 3 g/100 mL; OCTINOXATE 7 g/100 mL; OCTISALATE 3 g/100 mL; TITANIUM DIOXIDE 1.9 g/100 mL
INACTIVE INGREDIENTS: HEXAMETHYLDISILOXANE; WATER; ALCOHOL; CYCLOMETHICONE 5; ALKYL (C12-15) BENZOATE; DIETHYLAMINO HYDROXYBENZOYL HEXYL BENZOATE; CETYL PEG/PPG-10/1 DIMETHICONE (HLB 1.5); BUTYLENE GLYCOL; DICAPRYLYL CARBONATE; PHENOXYETHANOL; STEARIC ACID; SODIUM CHLORIDE; ALUMINUM HYDROXIDE; POLYHYDROXYSTEARIC ACID (2300 MW); ALUMINUM STEARATE; DIPROPYLENE GLYCOL; EDETATE DISODIUM; JASMINUM OFFICINALE FLOWER; ALOE VERA LEAF; PURSLANE; CHAMAEMELUM NOBILE FLOWER; BAMBUSA VULGARIS TOP; TOCOPHEROL

ACTIVE INGREDIENTS

AMILOXATE (3%)

OCTINOXATE (7%)

OCTISALATE (3%)

TITANIUM DIOXIDE (1.9%)

PURPOSE

SUNSCREEN

USES

- HELPS PREVENT SUNBURN.
- IF USED AS DIRECTED WITH OTHER SUN PROTECTION MEASURES (SEE DIRECTIONS), DECREASES THE RISK OF SKIN CANCER AND EARLY SKIN AGIN CAUSED BY THE SUN.

WARNINGS

FOR EXTERNAL USE ONLY.

DO NOT USE ON DAMAGED OR BROKEN SKIN.

WHEN USING THIS PRODUCT KEEP OUT OF EYES. RINSE WITH WATER TO REMOVE.

STOP USE AND ASK A DOCTOR IF SKIN RASH OCCURS.

KEEP OUT OF REACH OF CHILDREN.

IF PRODUCT IS SWALLOWED, GET MEIDCAL HELP OR CONTACT A POISON CONTROL CENTER RIGHT AWAY.

DIRECTIONS

- SHAKE WELL BEFORE USE.
- APPLY LIBERALLY 15 MINUTES BEFORE SUN EXPOSURE.
- REAPPLY:
- AFTER 40 MINUTES OF SWIMMING OR SWEATING
- IMMEDIATELY AFTER TOWEL DRYING
- AT LEAST EVERY 2 HOURS.
- SUN PROTECTION MEASURES. SPENDING TIME IN THE SUN INCREASES YOUR RISK OF SKIN CANCER AND EARLY SKIN AGING. TO DECREASE THIS RISK, REGULARLY USE A SUNSCREEN WITH A BROAD SPECTRUM SPF OF 15 OR HIGHER AND OTHER SUN PROTECTION MEASURES INCLUDING:
- LIMIT TIME IN THE SUN, ESPECIALLY FROM 10 AM - 2 PM
- WEAR LONG-SLEEVE SHIRTS, PANTS, HATS, AND SUNGLASSES
- CHILDREN UNDER 6 MONTHS. ASK A DOCTOR.

INACTIVE INGREDIENTS

DISILOXANE, WATER/AQUA/EAU, ALCOHOL, CYCLOPENTASILOXANE, C12-15 ALKYL BENZOATE, DIETHYLAMINO HYDROXYBENZOYL HEXYL BENZOATE, CETYL PEG/PPG-10/1 DIMETHICONE, BUTYLENE GLYCOL, DICAPRYLYL CARBONATE, PHENOXYETHANOL, STEARIC ACID, SODIUM CHLORIDE, ALUMINUM HYDROXIDE, POLYHYDROXYSTEARIC ACID, ALUMINUM STEARATE, DIPROPYLENE GLYCOL, DISODIUM EDTA, JASMINUM OFFICINALE (JASMINE) OIL, ALOE BARBADENSIS LEAF EXTRACT, PORTULACA OLERACEA EXTRACT, ANTHEMIS NOBILIS FLOWER EXTRACT, BAMBUSA VULGARIS EXTRACT, TOCOPHEROL. MADE IN KOREA.

OTHER INFORMATION

PROTECT THIS PRODUCT FROM EXCESSIVE HEAT AND DIRECT SUN.

QUESTIONS OR COMMENTS?

CALL TOLL FREE 1-800-792-5330